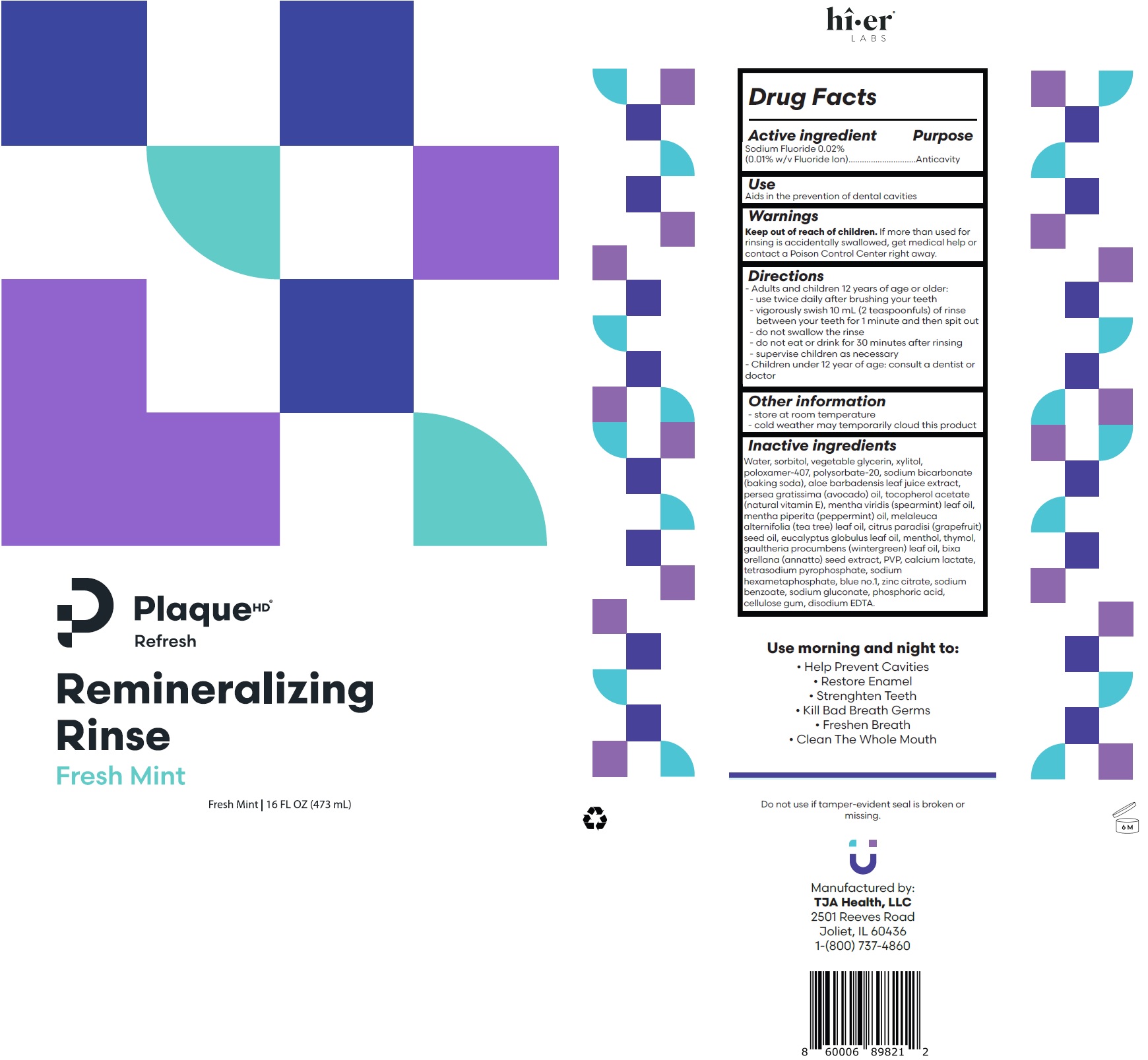 DRUG LABEL: Plaque Refresh Remineralizing Rinse Fresh Mint
NDC: 57660-003 | Form: LIQUID
Manufacturer: TJA Health LLC
Category: otc | Type: HUMAN OTC DRUG LABEL
Date: 20250530

ACTIVE INGREDIENTS: SODIUM FLUORIDE 0.1 mg/1 mL
INACTIVE INGREDIENTS: ALOE VERA LEAF; WATER; SORBITOL; GLYCERIN; XYLITOL; POLYSORBATE 20; SODIUM BICARBONATE; AVOCADO OIL; .ALPHA.-TOCOPHEROL ACETATE; SPEARMINT OIL; PEPPERMINT OIL; TEA TREE OIL; GRAPEFRUIT SEED OIL; EUCALYPTUS OIL; MENTHOL; THYMOL; METHYL SALICYLATE; BIXA ORELLANA SEED; POVIDONE, UNSPECIFIED; CALCIUM LACTATE; SODIUM PYROPHOSPHATE; HEXASODIUM HEXAMETAPHOSPHATE; SODIUM POLYMETAPHOSPHATE; FD&C BLUE NO. 1; ZINC CITRATE; SODIUM BENZOATE; SODIUM GLUCONATE; PHOSPHORIC ACID; CARBOXYMETHYLCELLULOSE SODIUM, UNSPECIFIED; EDETATE DISODIUM ANHYDROUS; POLOXAMER 407

Plaque Refresh Remineralizing Rinse Fresh Mint

Active ingredient

Sodium Fluoride 0.02% (0.01% w/v Fluoride Ion)

Purpose

Anticavity

Use

Aids in the prevention of dental cavities

Warnings

Keep out of reach of children.

If more than used for rinsing is accidentally swallowed, get medical help or contact a Poison Control Center right away.

Directions

- Adults and children 12 years of age or older:
- use twice daily after brushing your teeth
- vigorously swish 10 mL (2 teaspoonfuls) of rinse between your teeth for 1 minute and then spit out
- do not swallow the rinse
- do not eat or drink for 30 minutes after rinsing
- supervise children as necessary
- Children under 12 year of age: consult a dentist or doctor

Other information

- store at room temperature
- cold weather may temporarily cloud this product

Inactive ingredients

Water, sorbitol, vegetable glycerin, xylitol, poloxamer-407, polysorbate-20, sodium bicarbonate (baking soda), aloe barbadensis leaf juice extract, persea gratissima (avocado) oil, tocopherol acetate (natural vitamin E), mentha viridis (spearmint) leaf oil, mentha piperita (peppermint) oil, melaleuca alternifolia (tea tree) leaf oil, citrus paradisi (grapefruit) seed oil, eucalyptus globulus leaf oil, menthol, thymol, gaultheria procumbens (wintergreen) leaf oil, bixa orellana (annatto) seed extract, PVP, calcium lactate, tetrasodium pyrophosphate, sodium hexametaphosphate, blue no.1, zinc citrate, sodium benzoate, sodium gluconate, phosphoric acid, cellulose gum, disodium EDTA.